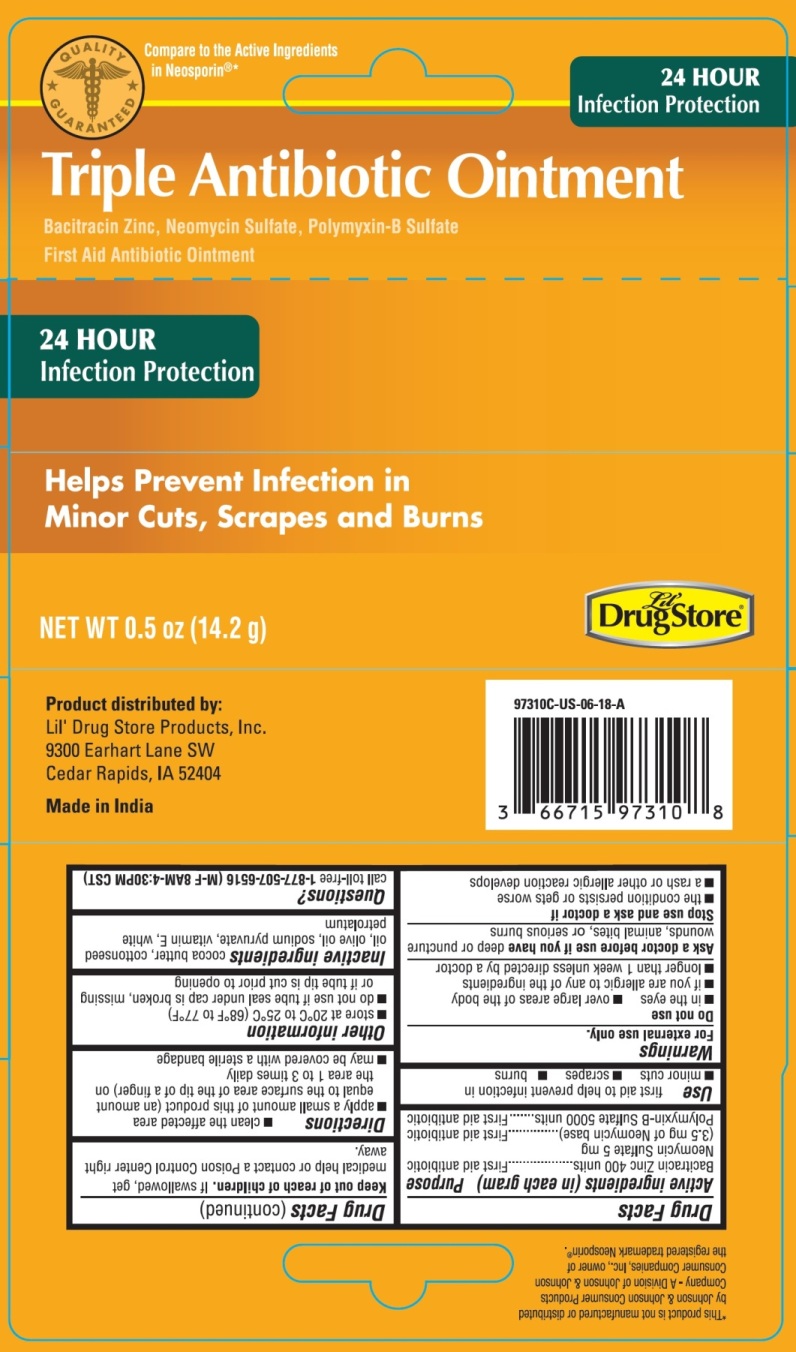 DRUG LABEL: Triple Antibiotic
NDC: 71927-003 | Form: OINTMENT
Manufacturer: Orazen Inc
Category: otc | Type: HUMAN OTC DRUG LABEL
Date: 20220224

ACTIVE INGREDIENTS: BACITRACIN ZINC 400 [USP'U]/1 g; NEOMYCIN SULFATE 3.5 mg/1 g; POLYMYXIN B SULFATE 5000 [USP'U]/1 g
INACTIVE INGREDIENTS: COCOA BUTTER; COTTONSEED OIL; OLIVE OIL; SODIUM PYRUVATE; .ALPHA.-TOCOPHEROL ACETATE; PETROLATUM

Triple Antibiotic

Active Ingredients (in each gram)

Bacitracin Zinc 400 units

Neomycin Sulfate 5 mg

(3.5 mg of Neomycin base)

Polymyxin B Sulfate 5000 units

Purpose

First aid antibiotic

Uses

first aid to help prevent infection in

- minor cuts
- scrapes
- burns

Warnings

For external use only.

Do not use

- in the eyes
- if you are allergic to any of the ingredients
- longer than 1 week unless directed by a doctor
- over large areas of the body

Ask a doctor before use if you have deep or puncture wounds, animal bites, or serious burns

Stop use and ask a doctor if

- the condition persists or gets worse
- a rash or other allergic reaction develops

Keep out of reach of children. If swallowed, get medical help or contact a Poison Control Center right away.

Directions

- clean the affected area
- apply a small amount of this product (an amount equal to the surface area of the tip of a finger) on the area 1 to 3 times daily
- may be covered with a sterile bandage

Other Information

- store at room temperature 20°C to 25°C (68°F to 77°C)
- do not use if tube seal under cap is broken, missing or if tube tip is cut prior to opening

Inactive Ingredients

cocoa butter, cottonseed oil, olive oil, sodium pyruvate, vitamin E, white petrolatum

PACKAGE LABEL

PRINCIPAL DISPLAY PANEL

Triple Antibiotic Ointment

Bacitracin Zinc, Neomycin Sulfate and Polymyxin B Sulfate

First Aid Antibiotic Ointment

NET WT 0.5 oz (14.2 g)